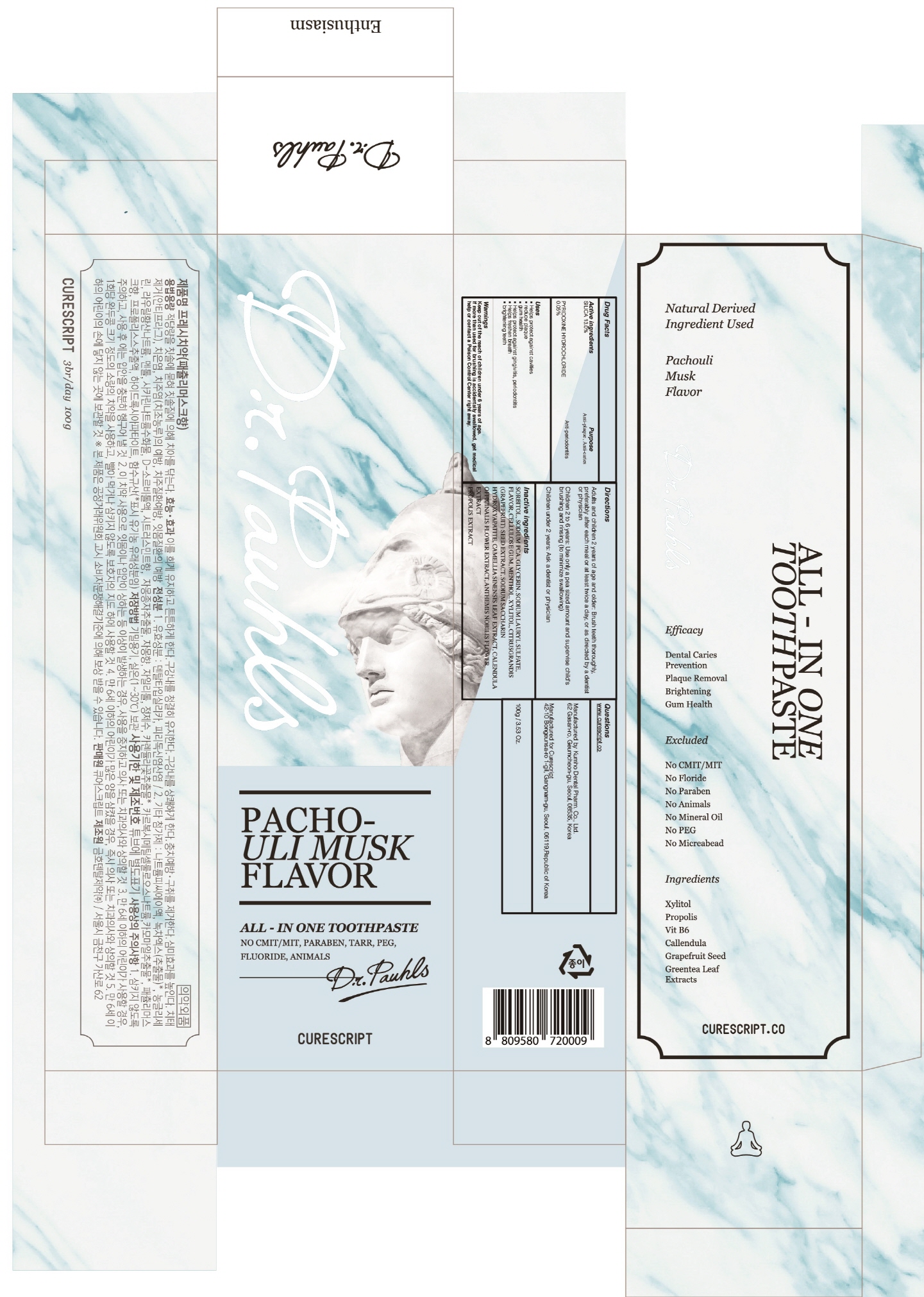 DRUG LABEL: Dr.Pauhls TOOTHPAST E PATCHOULI MUSK FLAVOR
NDC: 72265-020 | Form: PASTE, DENTIFRICE
Manufacturer: CURESCRIPT
Category: otc | Type: HUMAN OTC DRUG LABEL
Date: 20180726

ACTIVE INGREDIENTS: SILICON DIOXIDE 13.0 g/100 g; PYRIDOXINE HYDROCHLORIDE 0.05 g/100 g
INACTIVE INGREDIENTS: SORBITOL; SODIUM PYRROLIDONE CARBOXYLATE

ACTIVE INGREDIENT

Active ingredients: SILICA 13.0%, PYRIDOXINE HYDROCHLORIDE 0.05%

INACTIVE INGREDIENT

Inactive ingredients:

SORBITOL, SODIUM PCA, GLYCERIN, SODIUM LAURYL SULFATE, FLAVOR, CELLULOSE GUM, MENTHOL, XYLITOL, CITRUSGRANDIS (GRAPEFRUIT) SEED EXTRACT, SODIUM SACCHARIN HYDROXYAPATITE, CAMELLIA SINENSIS LEAF EXTRACT, CALENDULA OFFICINALIS FLOWER EXTRACT, ANTHEMIS NOBILIS FLOWER EXTRACT PROPOLIS EXTRACT

PURPOSE

Purpose: Anti-plaque, Anti-caries, Anti-periodontitis

WARNINGS

Keep out of the reach of children under 6 years of age.

If more than used for brushing is accidentally swallowed, get medical help or contact a Poison Control Center right away.

KEEP OUT OF REACH OF CHILDREN

Keep out of the reach of children under 6 years of age.

Uses

- Helps protect against cavities

- reduce plaque

- gum health

- Helps protect against gingivitis, periodontitis

- Helps freshen breath

- brightening teeth

Directions

Adults and children 2 years of age and older: Brush teeth thoroughly, preferably after each meal or at least twice a day, or as directed by a dentist or physician

Children 2 to 6 years: Use only a pea sized amount and supervise child's brushing and rinsing (to minimize swallowing)

Children under 2 years: Ask a dentist or physician